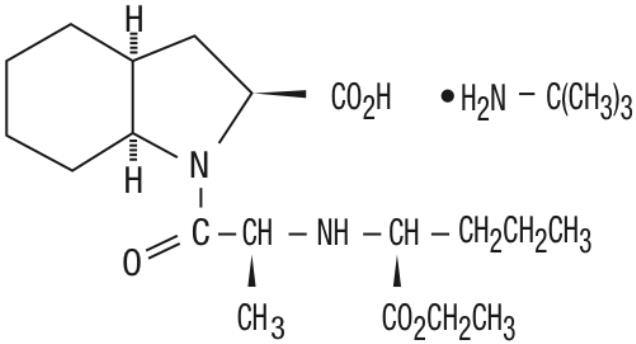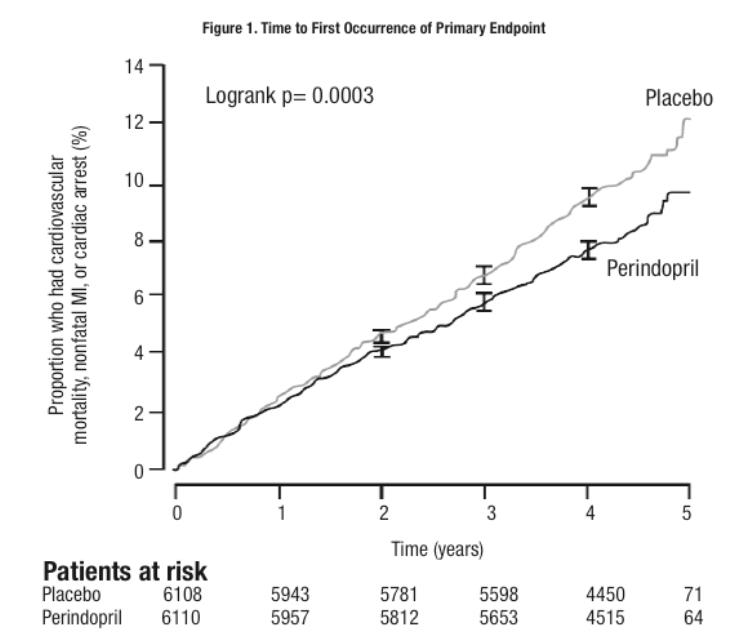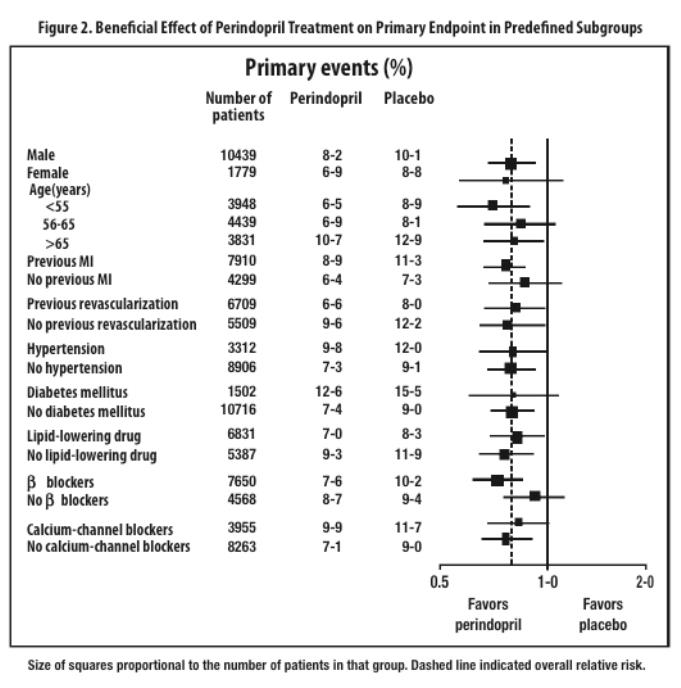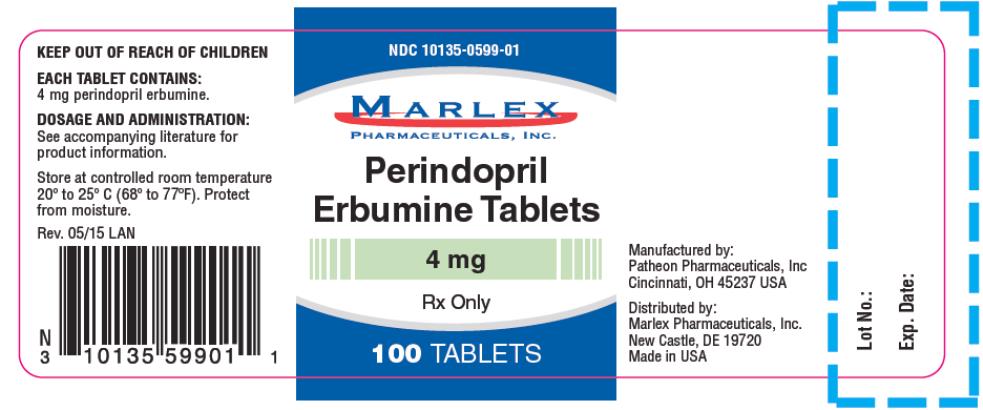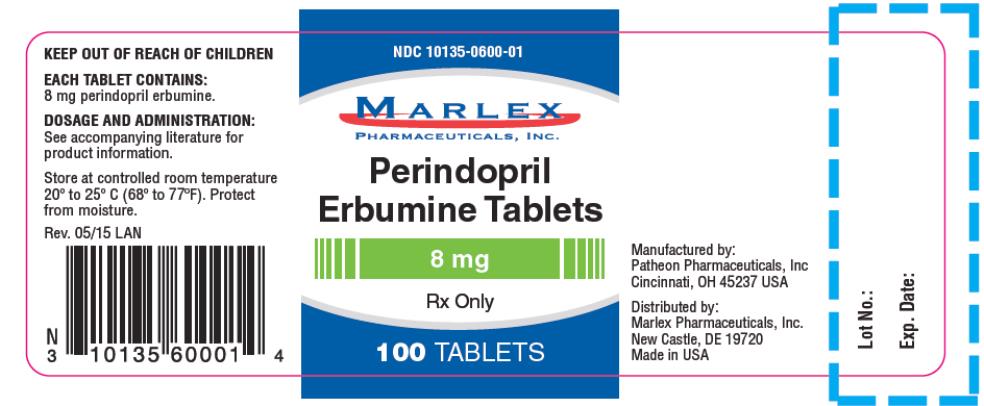 DRUG LABEL: Perindopril Erbumine
NDC: 10135-599 | Form: TABLET
Manufacturer: Marlex Pharmaceuticals Inc
Category: prescription | Type: HUMAN PRESCRIPTION DRUG LABEL
Date: 20150528

ACTIVE INGREDIENTS: PERINDOPRIL ERBUMINE 4 mg/1 1
INACTIVE INGREDIENTS: SILICON DIOXIDE; LACTOSE; MAGNESIUM STEARATE; CELLULOSE, MICROCRYSTALLINE; FERRIC OXIDE RED

HIGHLIGHTS OF PRESCRIBING INFORMATION

These highlights do not include all the information needed to use Perindopril Erbumine Tablets safely and effectively. See full prescribing information for Perindopril Erbumine Tablets.
Perindopril Erbumine 4 and 8 mg Tablets
Initial U.S. Approval: 1993

RECENT MAJOR CHANGES

• Drug Interaction Dual Blockade of the Renin-Angiotensin System (7.8) 03/2013

WARNING: FETAL TOXICITY

See full prescribing information for complete boxed warning.

- When pregnancy is detected, discontinue Perindopril Erbumine Tablets as soon as possible. (5.4)
- Drugs that act directly on the renin-angiotensin system can cause injury and death to the developing fetus. (5.4)

1 INDICATIONS AND USAGE

• Perindopril Erbumine Tablets are indicated for the treatment of patients with essential hypertension (1.1)

• Perindopril Erbumine Tablets are indicated for treatment of patients with stable coronary artery disease to reduce the risk of cardiovascular mortality or nonfatal myocardial infarction (1.2)

2 DOSAGE AND ADMINISTRATION

Hypertension

• The recommended initial dose is 4 mg once a day. The dosage may be titrated upward until blood pressure, when measured just before the next dose, is controlled or to a maximum of 16 mg per day (2.1)

Stable Coronary Artery Disease

• Perindopril Erbumine should be given at an initial dose of 4 mg once daily for 2 weeks, and then increased, as tolerated, to a maintenance dose of 8 mg once daily (2.2)

3 DOSAGE FORMS AND STRENGTHS

• Tablets: 4 and 8 mg (3)

4 CONTRAINDICATIONS

• Angioedema related to previous treatment with an ACE inhibitor, or a history of hereditary or idiopathic angioedema (4.0, 5.1)

• Do not co-administer aliskiren with Perindopril Erbumine in patients with diabetes (4.0, 7.8)

5 WARNINGS AND PRECAUTIONS

• Watch for anaphylactoid reactions, including angioedema (5.1)

• Monitor renal function during therapy (5.8)

• Assess for hypotension and hyperkalemia (5.2, 5.6)

6 ADVERSE REACTIONS

• Hypertension: Most common adverse events (incidence greater than or equal to 5%) are cough, dizziness and back pain (6.1)

• Stable Coronary Artery Disease: Most common adverse events leading to discontinuation were cough, drug intolerance, and hypotension (6.1)

To report SUSPECTED ADVERSE REACTIONS, contact Lannett Company, Inc. at 1-800-325-9994 or FDA at 1-800-FDA-1088 or www.FDA.gov/Medwatch.

7 DRUG INTERACTIONS

• Diuretics: Excessive drop in blood pressure (7.1)

• Potassium-sparing diuretics/potassium supplements: Hyperkalemia (7.2)

• Lithium: Increase serum lithium levels, symptoms of lithium toxicity (7.3)

• Injectable gold: Nitritoid reactions (facial flushing, nausea, vomiting, and hypotension) (7.4)

• NSAID use may lead to increased risk of renal impairment and loss of antihypertensive effect (7.7)

• Dual inhibition of the renin-angiotensin system: Increased risk of renal impairment, hypotension, and hyperkalemia (7.8).

8 USE IN SPECIFIC POPULATIONS

• Geriatrics: Start at low daily dose (4 mg or less) and titrate slowly as needed. Experience with doses exceeding 8 mg is limited (8.5)

• Dosage adjustment may be necessary in renally impaired patients (8.7)

FULL PRESCRIBING INFORMATION

WARNING: FETAL TOXICITY

- When pregnancy is detected, discontinue Perindopril Erbumine Tablets as soon as possible. (5.4)
- Drugs that act directly on the renin-angiotensin system can cause injury and death to the developing fetus. (5.4)

1 INDICATIONS AND USAGE

1.1 Hypertension

Perindopril Erbumine Tablets are indicated for the treatment of patients with essential hypertension. Perindopril Erbumine Tablets may be used alone or given with other classes of antihypertensives, especially thiazide diuretics.

1.2 Stable Coronary Artery Disease

Perindopril Erbumine Tablets are indicated for treatment of patients with stable coronary artery disease to reduce the risk of cardiovascular mortality or nonfatal myocardial infarction. Perindopril Erbumine Tablets can be used with conventional treatment for management of coronary artery disease, such as antiplatelet, antihypertensive or lipid-lowering therapy.

2 DOSAGE AND ADMINISTRATION

2.1 Hypertension

Use in Uncomplicated Hypertensive Patients: In patients with essential hypertension, the recommended initial dose is 4 mg once a day. The dose may be titrated, as needed to a maximum of 16 mg per day. The usual maintenance dose range is 4 mg to 8 mg administered as a single daily dose or in two divided doses.

Use in Elderly Patients: The recommended initial daily dosage of Perindopril Erbumine for the elderly is
4 mg daily, given in one or two divided doses. Experience with Perindopril Erbumine is limited in the elderly at doses exceeding 8 mg. Dosages above 8 mg should be administered with careful blood pressure monitoring and dose titration [see Use in Specific Populations (8.5)].

Use with Diuretics: In patients who are currently being treated with a diuretic, symptomatic hypotension can occur following the initial dose of Perindopril Erbumine. Consider reducing the dose of diuretic prior to starting Perindopril Erbumine [see Drug Interactions (7.1)].

2.2 Stable Coronary Artery Disease

In patients with stable coronary artery disease, Perindopril Erbumine should be given at an initial dose of
4 mg once daily for 2 weeks, and then increased as tolerated, to a maintenance dose of 8 mg once daily. In elderly patients (greater than 70 years), Perindopril Erbumine should be given as a 2 mg dose once daily in the first week, followed by 4 mg once daily in the second week and 8 mg once daily for maintenance dose if tolerated.

2.3 Dose Adjustment in Renal Impairment and Dialysis

Perindoprilat elimination is decreased in renally impaired patients. Perindopril Erbumine is not recommended in patients with creatinine clearance <30 mL/min. For patients with lesser degrees of impairment, the initial dosage should be 2 mg/day and dosage should not exceed 8 mg/day.

During dialysis, perindopril is removed with the same clearance as in patients with normal renal function.

3 DOSAGE FORMS AND STRENGTHS

Tablets are oblong with a score on one side.

4 mg tablet is pink and debossed on the unscored side with “ACN 4”.

8 mg tablet is salmon and debossed on the unscored side with “ACN 8”.

4 CONTRAINDICATIONS

Perindopril Erbumine Tablets are contraindicated in patients known to be hypersensitive (including angioedema) to this product or to any other ACE inhibitor. Perindopril Erbumine Tablets are also contraindicated in patients with hereditary or idiopathic angioedema.

Do not co-administer aliskiren with Perindopril Erbumine in patients with diabetes [see Drug Interactions (7.8)].

5 WARNINGS AND PRECAUTIONS

5.1 Anaphylactoid and Possibly Related Reactions

Presumably because angiotensin-converting enzyme inhibitors affect the metabolism of eicosanoids and polypeptides, including endogenous bradykinin, patients receiving ACE inhibitors (including Perindopril Erbumine) may be subject to a variety of adverse events, some of them serious. Black patients receiving ACE inhibitors have a higher incidence of angioedema compared to nonblacks.

Head and Neck Angioedema: Angioedema of the face, extremities, lips, tongue, glottis, or larynx has been reported in patients treated with ACE inhibitors, including Perindopril Erbumine (0.1% of patients treated with Perindopril Erbumine in U.S. clinical trials). Angioedema associated with involvement of the tongue, glottis or larynx may be fatal. In such cases, discontinue Perindopril Erbumine treatment immediately and observe until the swelling disappears. When involvement of the tongue, glottis, or larynx appears likely to cause airway obstruction, administer appropriate therapy, such as subcutaneous epinephrine solution 1:1000 (0.3 to 0.5 mL), promptly.

Intestinal Angioedema: Intestinal angioedema has been reported in patients treated with ACE inhibitors. These patients presented with abdominal pain (with or without nausea or vomiting); in some cases there was no prior history of facial angioedema and C-1 esterase levels were normal. The angioedema was diagnosed by procedures including abdominal CT scan or ultrasound, or at surgery, and symptoms resolved after stopping the ACE inhibitor. Intestinal angioedema should be included in the differential diagnosis of patients on ACE inhibitors presenting with abdominal pain.

5.2 Hypotension

Perindopril Erbumine can cause symptomatic hypotension. Perindopril Erbumine has been associated with hypotension in 0.3% of uncomplicated hypertensive patients in U.S. placebo-controlled trials. Symptoms related to orthostatic hypotension were reported in another 0.8% of patients.

Symptomatic hypotension is most likely to occur in patients who have been volume or salt-depleted as a result of prolonged diuretic therapy, dietary salt restriction, dialysis, diarrhea or vomiting [see Dosage and Administration (2.1)].

ACE inhibitors may cause excessive hypotension, and may be associated with oliguria or azotemia, and rarely with acute renal failure and death. In patients with ischemic heart disease or cerebrovascular disease, an excessive fall in blood pressure could result in a myocardial infarction or a cerebrovascular accident.

In patients at risk of excessive hypotension, Perindopril Erbumine therapy should be started under very close medical supervision. Patients should be followed closely for the first two weeks of treatment and whenever the dose of Perindopril Erbumine and/or diuretic is increased.

If excessive hypotension occurs, the patient should be placed immediately in a supine position and, if necessary, treated with an intravenous infusion of physiological saline. Perindopril Erbumine treatment can usually be continued following restoration of volume and blood pressure.

5.3 Neutropenia/Agranulocytosis

ACE inhibitors have been associated with agranulocytosis and bone marrow depression, most frequently in patients with renal impairment, especially patients with a collagen vascular disease such as systemic lupus erythematosus or scleroderma.

5.4 Fetal Toxicity

Pregnancy Category D

Use of drugs that act on the renin-angiotensin system during the second and third trimesters of pregnancy reduces fetal renal function and increases fetal and neonatal morbidity and death. Resulting oligohydramnios can be associated with fetal lung hypoplasia and skeletal deformations. Potential neonatal adverse effects include skull hypoplasia, anuria, hypotension, renal failure, and death. When pregnancy is detected discontinue Perindopril Erbumine Tablets as soon as possible [see Use in Specific Populations (8.1)].

5.5 Impaired Renal Function

As a consequence of inhibiting the renin-angiotensin-aldosterone system, changes in renal function may be anticipated in susceptible individuals. Renal function should be monitored periodically in patients receiving Perindopril Erbumine [see Dosage and Administration (2.3)], [see Drug Interactions (7.8)].

In patients with severe congestive heart failure, where renal function may depend on the activity of the renin-angiotensin-aldosterone system, treatment with ACE inhibitors, including Perindopril Erbumine, may be associated with oliguria, progressive azotemia, and, rarely, acute renal failure and death.

In hypertensive patients with unilateral or bilateral renal artery stenosis, increases in blood urea nitrogen and serum creatinine may occur; usually reversible upon discontinuation of the ACE inhibitor. In such patients, renal function should be monitored during the first few weeks of therapy.

Some Perindopril Erbumine-treated patients have developed minor and transient increases in blood urea nitrogen and serum creatinine especially in those concomitantly treated with a diuretic.

5.6 Hyperkalemia

Elevations of serum potassium have been observed in some patients treated with ACE inhibitors, including Perindopril Erbumine. Most cases were isolated single values that did not appear clinically relevant and were rarely a cause for withdrawal. Risk factors for the development of hyperkalemia include renal insufficiency, diabetes mellitus and the concomitant use of agents such as potassium-sparing diuretics, potassium supplements and/or potassium-containing salt substitutes [see Drug Interactions (7.2)].

Serum potassium should be monitored periodically in patients receiving Perindopril Erbumine.

5.7 Cough

Presumably because of the inhibition of the degradation of endogenous bradykinin, persistent nonproductive cough has been reported with all ACE inhibitors, generally resolving after discontinuation of therapy. Consider ACE inhibitor-induced cough in the differential diagnosis of cough.

5.8 Hepatic Failure

Rarely, ACE inhibitors have been associated with a syndrome that starts with cholestatic jaundice and progresses to fulminant hepatic necrosis and sometimes death. The mechanism of this syndrome is not understood. Patients receiving ACE inhibitors who develop jaundice or marked elevations of hepatic enzymes should discontinue the ACE inhibitor and receive appropriate medical follow-up.

5.9 Surgery/Anesthesia

In patients undergoing surgery or during anesthesia with agents that produce hypotension, Perindopril Erbumine may block angiotensin II formation that would otherwise occur secondary to compensatory renin release. Hypotension attributable to this mechanism can be corrected by volume expansion.

6 ADVERSE REACTIONS

Because clinical trials are conducted under widely varying conditions, adverse event rates observed in the clinical trials of a drug cannot be directly compared to rates in the clinical trials of another drug and may not reflect the rates observed in practice.

6.1 Clinical Trials Experience

The following adverse reactions are discussed elsewhere in labeling:

• Anaphylactoid reactions, including angioedema [see Warnings and Precautions (5.1)]

• Hypotension [see Warnings and Precautions (5.2)]

• Neutropenia and agranulocytosis [see Warnings and Precautions (5.3)]

• Impaired renal function [see Warnings and Precautions (5.5)]

• Hyperkalemia [see Warnings and Precautions (5.6)]

• Cough [see Warnings and Precautions (5.7)]

Hypertension

Perindopril Erbumine has been evaluated for safety in approximately 3,400 patients with hypertension in U.S. and foreign clinical trials. The data presented here are based on results from the 1,417 Perindopril Erbumine-treated patients who participated in the U.S. clinical trials. Over 220 of these patients were treated with Perindopril Erbumine for at least one year.

In placebo-controlled U.S. clinical trials, the incidence of premature discontinuation of therapy due to adverse events was 6.5% in patients treated with Perindopril Erbumine and 6.7% in patients treated with placebo. The most common causes were cough, headache, asthenia and dizziness.

Among 1,012 patients in placebo-controlled U.S. trials, the overall frequency of reported adverse events was similar in patients treated with Perindopril Erbumine and in those treated with placebo (approximately 75% in each group). The only adverse events whose incidence on Perindopril Erbumine was at least 2% greater than on placebo were cough (12% vs. 4.5%) and back pain (5.8% vs. 3.1%).

Dizziness was not reported more frequently in the perindopril group (8.2%) than in the placebo group (8.5%), but its likelihood increased with dose, suggesting a causal relationship with perindopril.

Stable Coronary Artery Disease

Perindopril has been evaluated for safety in EUROPA, a double-blind, placebo-controlled study in
12,218 patients with stable coronary artery disease. The overall rate of discontinuation was about 22% on drug and placebo. The most common medical reasons for discontinuation that were more frequent on perindopril than placebo were cough, drug intolerance and hypotension.

6.2 Postmarketing Experience

Voluntary reports of adverse events in patients taking Perindopril Erbumine Tablets that have been received since market introduction and are of unknown causal relationship to Perindopril Erbumine Tablets include: cardiac arrest, eosinophilic pneumonitis, neutropenia/agranulocytosis, pancytopenia, anemia (including hemolytic and aplastic), thrombocytopenia, acute renal failure, nephritis, hepatic failure, jaundice (hepatocellular or cholestatic), symptomatic hyponatremia, bullous pemphigoid, pemphigus, acute pancreatitis, falls, psoriasis, exfoliative dermatitis and a syndrome which may include: arthralgia/arthritis, vasculitis, serositis, myalgia, fever, rash or other dermatologic manifestations, a positive antinuclear antibody (ANA), leukocytosis, eosinophilia or an elevated erythrocyte sedimentation rate (ESR).

6.3 Clinical Laboratory Test Findings

Hematology: Small decreases in hemoglobin and hematocrit occur frequently in hypertensive patients treated with Perindopril Erbumine, but are rarely of clinical importance. In controlled clinical trials, no patient was discontinued from therapy due to the development of anemia. Leukopenia (including neutropenia) was observed in 0.1% of patients in U.S. clinical trials [see Warnings and Precautions (5.3)].

Liver Function Tests: Elevations in ALT (1.6% Perindopril Erbumine versus 0.9% placebo) and AST (0.5% Perindopril Erbumine versus 0.4% placebo) have been observed in placebo-controlled clinical trials. The elevations were generally mild and transient and resolved after discontinuation of therapy.

7 DRUG INTERACTIONS

7.1 Diuretics

Patients on diuretics, and especially those started recently, may occasionally experience an excessive reduction of blood pressure after initiation of Perindopril Erbumine therapy. The possibility of hypotensive effects can be minimized by either decreasing the dose of or discontinuing the diuretic or increasing the salt intake prior to initiation of treatment with perindopril. If diuretic therapy cannot be altered, provide close medical supervision with the first dose of Perindopril Erbumine, for at least two hours and until blood pressure has stabilized for another hour [see Warnings and Precautions (5.2)].

The rate and extent of perindopril absorption and elimination are not affected by concomitant diuretics. The bioavailability of perindoprilat was reduced by diuretics, however, and this was associated with a decrease in plasma ACE inhibition.

7.2 Potassium Supplements and Potassium-Sparing Diuretics

Perindopril Erbumine may increase serum potassium because of its potential to decrease aldosterone production. Use of potassium-sparing diuretics (spironolactone, amiloride, triamterene and others), potassium supplements or other drugs capable of increasing serum potassium (indomethacin, heparin, cyclosporine and others) can increase the risk of hyperkalemia. Therefore, if concomitant use of such agents is indicated, monitor the patient’s serum potassium frequently.

7.3 Lithium

Increased serum lithium and symptoms of lithium toxicity have been reported in patients receiving concomitant lithium and ACE inhibitor therapy. Frequent monitoring of serum lithium concentration is recommended. Use of a diuretic may further increase the risk of lithium toxicity.

7.4 Gold

Nitritoid reactions (symptoms include facial flushing, nausea, vomiting and hypotension) have been reported rarely in patients on therapy with injectable gold (sodium aurothiomalate) and concomitant ACE Inhibitor therapy including Perindopril Erbumine.

7.5 Digoxin

A controlled pharmacokinetic study has shown no effect on plasma digoxin concentrations when coadministered with Perindopril Erbumine, but an effect of digoxin on the plasma concentration of perindopril/perindoprilat has not been excluded.

7.6 Gentamicin

Animal data have suggested the possibility of interaction between perindopril and gentamicin. However, this has not been investigated in human studies.

7.7 Non-Steroidal Anti-Inflammatory Agents including Selective Cyclooxygenase-2 Inhibitors (COX-2 Inhibitors)

In patients who are elderly, volume-depleted (including those on diuretic therapy), or with compromised renal function, co-administration of NSAIDs, including selective COX-2 inhibitors, with ACE inhibitors, including perindopril, may result in deterioration of renal function, including possible acute renal failure. These effects are usually reversible. Monitor renal function periodically in patients receiving perindopril and NSAID therapy.

The antihypertensive effect of ACE inhibitors, including perindopril, may be attenuated by NSAIDs including selective COX-2 inhibitors.

7.8 Dual Blockade of the Renin-Angiotensin System (RAS)

Dual blockade of the RAS with angiotensin receptor blockers, ACE inhibitors, or aliskiren is associated with increased risks of hypotension, hyperkalemia, and changes in renal function (including acute renal failure) compared to monotherapy. Closely monitor blood pressure, renal function and electrolytes in patients on Perindopril Erbumine and other agents that affect the RAS.

Do not co-administer aliskiren with Perindopril Erbumine in patients with diabetes. Avoid use of aliskiren with Perindopril Erbumine in patients with renal impairment (GFR <60 ml/min).

8 USE IN SPECIFIC POPULATIONS

8.1 Pregnancy

Pregnancy Category D [see Boxed Warning and Warnings and Precautions (5.4)].

Use of drugs that act on the renin-angiotensin system during the second and third trimesters of pregnancy reduces fetal renal function and increases fetal and neonatal morbidity and death. Resulting oligohydramnios can be associated with fetal lung hypoplasia and skeletal deformations. Potential neonatal adverse effects include skull hypoplasia, anuria, hypotension, renal failure, and death. When pregnancy is detected, discontinue Perindopril Erbumine Tablets as soon as possible. These adverse outcomes are usually associated with use of these drugs in the second and third trimester of pregnancy. Most epidemiologic studies examining fetal abnormalities after exposure to antihypertensive use in the first trimester have not distinguished drugs affecting the renin-angiotensin system from other antihypertensive agents. Appropriate management of maternal hypertension during pregnancy is important to optimize outcomes for both mother and fetus.

In the unusual case that there is no appropriate alternative to therapy with drugs affecting the renin-angiotensin system for a particular patient, apprise the mother of the potential risk to the fetus. Perform serial ultrasound examinations to assess the intra-amniotic environment. If oligohydramnios is observed, discontinue Perindopril Erbumine Tablets, unless it is considered lifesaving for the mother. Fetal testing may be appropriate, based on the week of pregnancy. Patients and physicians should be aware, however, that oligohydramnios may not appear until after the fetus has sustained irreversible injury. Closely observe infants with histories of in utero exposure to Perindopril Erbumine for hypotension, oliguria, and hyperkalemia [see Use in Specific Populations (8.4)].

Radioactivity was detectable in fetuses after administration of ^14C-perindopril to pregnant rats.

8.3 Nursing Mothers

Milk of lactating rats contained radioactivity following administration of C-perindopril. It is not known whether perindopril is secreted in human milk. Because many drugs are secreted in human milk, caution should be exercised when Perindopril Erbumine Tablets are given to nursing mothers.

8.4 Pediatric Use

Neonates with a history of in utero exposure to Perindopril Erbumine:

If oliguria or hypotension occurs, direct attention toward support of blood pressure and renal perfusion. Exchange transfusions or dialysis may be required as a means of reversing hypotension and/or substituting for disordered renal function.

Perindopril, which crosses the placenta, can theoretically be removed from the neonatal circulation by these means, but limited experience has not shown that such removal is central to the treatment of these infants.

Safety and effectiveness of Perindopril Erbumine Tablets in pediatric patients have not been established.

8.5 Geriatric Use

The mean blood pressure effect of perindopril was somewhat smaller in patients over 60 than in younger patients, although the difference was not significant. Plasma concentrations of both perindopril and perindoprilat were increased in elderly patients compared to concentrations in younger patients. No adverse effects were clearly increased in older patients with the exception of dizziness and possibly rash.

Start at a low dose and titrate slowly as needed. Monitor for dizziness because of potential for falls.

Experience with Perindopril Erbumine Tablets in elderly patients at daily doses exceeding 8 mg is limited.

8.6 Renal Impairment

Dosage adjustment may be necessary in renally impaired patients [see Dosage and Administration (2.3) and Clinical Pharmacology (12.3)].

8.7 Hepatic Impairment

The bioavailability of perindoprilat is increased in patients with impaired hepatic function [see Clinical Pharmacology (12.3)].

10 OVERDOSAGE

In animals, doses of perindopril up to 2,500 mg/kg in mice, 3,000 mg/kg in rats and 1,600 mg/kg in dogs were non-lethal. Past experiences were scant but suggested that overdosage with other ACE inhibitors was also fairly well tolerated by humans. The most likely manifestation is hypotension, and treatment should be symptomatic and supportive. Therapy with the ACE inhibitor should be discontinued, and the patient should be observed. Dehydration, electrolyte imbalance and hypotension should be treated by established procedures.

Among the reported cases of perindopril overdosage, patients who were known to have ingested a dose of 80 mg to 120 mg required assisted ventilation and circulatory support. One additional patient developed hypothermia, circulatory arrest and died following ingestion of up to 180 mg of perindopril. The intervention for perindopril overdose may require vigorous support.

Laboratory determinations of serum levels of perindopril and its metabolites are not widely available, and such determinations have, in any event, no established role in the management of perindopril overdose. No data are available to suggest physiological maneuvers (e.g., maneuvers to change the pH of the urine) that might accelerate elimination of perindopril and its metabolites. Perindopril can be removed by hemodialysis, with clearance of 52 mL/min for perindopril and 67 mL/min for perindoprilat.

Angiotensin II could presumably serve as a specific antagonist-antidote in the settling of perindopril overdose, but angiotensin II is essentially unavailable outside of scattered research facilities. Because the hypotensive effect of perindopril is achieved through vasodilation and effective hypovolemia, it is reasonable to treat perindopril overdose by infusion of normal saline solution.

11 DESCRIPTION

Perindopril Erbumine Tablets contain the tert-butylamine salt of perindopril, the ethyl ester of a
non-sulfhydryl angiotensin-converting enzyme (ACE) inhibitor. Perindopril erbumine is chemically described as (2S,3αS,7αS)-1-[(S)-N-[(S)-1-Carboxy-butyl]alanyl]hexahydro-2-indolinecarboxylic acid, 1-ethyl ester, compound with tert-butylamine (1:1). Its molecular formula is C19H32N2O5C4H11N. Its structural formula is:

Perindopril erbumine is a white, crystalline powder with a molecular weight of 368.47 (free acid) or 441.61 (salt form). It is freely soluble in water (60% w/w), alcohol and chloroform.

Perindopril is the free acid form of perindopril erbumine, is a pro-drug and metabolized in vivo by hydrolysis of the ester group to form perindoprilat, the biologically active metabolite.

Perindopril Erbumine Tablets are available in 4 mg and 8 mg strengths for oral administration. In addition to perindopril erbumine, each tablet contains the following inactive ingredients: colloidal silica (hydrophobic), lactose, magnesium stearate and microcrystalline cellulose. The 4 mg and 8 mg tablets also contain iron oxide.

12 CLINICAL PHARMACOLOGY

12.1 Mechanism of Action

Perindopril Erbumine is a pro-drug for perindoprilat, which inhibits ACE in human subjects and animals. The mechanism through which perindoprilat lowers blood pressure is believed to be primarily inhibition of ACE activity. ACE is a peptidyl dipeptidase that catalyzes conversion of the inactive decapeptide, angiotensin I, to the vasoconstrictor, angiotensin II.

Angiotensin II is a potent peripheral vasoconstrictor, which stimulates aldosterone secretion by the adrenal cortex, and provides negative feedback on renin secretion. Inhibition of ACE results in decreased plasma angiotensin II, leading to decreased vasoconstriction, increased plasma renin activity and decreased aldosterone secretion. The latter results in diuresis and natriuresis and may be associated with a small increase of serum potassium.

ACE is identical to kininase II, an enzyme that degrades bradykinin. Whether increased levels of bradykinin, a potent vasodepressor peptide, play a role in the therapeutic effects of Perindopril Erbumine remains to be elucidated.

While the principal mechanism of perindopril in blood pressure reduction is believed to be through the renin-angiotensin-aldosterone system, ACE inhibitors have some effect even in apparent low-renin hypertension. Perindopril has been studied in relatively few black patients, usually a low-renin population, and the average response of diastolic blood pressure to perindopril was about half the response seen in nonblack patients, a finding consistent with previous experience of other ACE inhibitors.

12.2 Pharmacodynamics

After administration of perindopril, ACE is inhibited in a dose and blood concentration-related fashion, with the maximal inhibition of 80 to 90% attained by 8 mg persisting for 10 to 12 hours. Twenty-four hour ACE inhibition is about 60% after these doses. The degree of ACE inhibition achieved by a given dose appears to diminish over time (the ID increases). The pressor response to an angiotensin I infusion is reduced by perindopril, but this effect is not as persistent as the effect on ACE; there is about 35% inhibition at 24 hours after a 12 mg dose.

12.3 Pharmacokinetics

Absorption: Oral administration of Perindopril Erbumine results in peak plasma concentrations that occur at approximately 1 hour. The absolute oral bioavailability of perindopril is about 75%. Following absorption, approximately 30 to 50% of systemically available perindopril is hydrolyzed to its active metabolite, perindoprilat, which has a mean bioavailability of about 25%. Peak plasma concentrations of perindoprilat are attained 3 to 7 hours after perindopril administration. Oral administration of Perindopril Erbumine with food does not significantly lower the rate or extent of perindopril absorption relative to the fasted state. However, the extent of biotransformation of perindopril to the active metabolite, perindoprilat, is reduced approximately 43%, resulting in a reduction in the plasma ACE inhibition curve of approximately 20%, probably clinically insignificant. In clinical trials, perindopril was generally administered in a non-fasting state.

With 4 mg, 8 mg and 16 mg doses of Perindopril Erbumine, Cmax and AUC of perindopril and perindoprilat increase in a dose-proportional manner following both single oral dosing and at steady state during a
once-a-day multiple dosing regimen.

Distribution: Approximately 60% of circulating perindopril is bound to plasma proteins, and only 10 to 20% of perindoprilat is bound. Therefore, drug interactions mediated through effects on protein binding are not anticipated.

Metabolism and Elimination: Following oral administration perindopril exhibits multicompartment pharmacokinetics including a deep tissue compartment (ACE binding sites). The mean half-life of perindopril associated with most of its elimination is approximately 0.8 to 1 hours.

Perindopril is extensively metabolized following oral administration, with only 4 to 12% of the dose recovered unchanged in the urine. Six metabolites resulting from hydrolysis, glucuronidation and cyclization via dehydration have been identified. These include the active ACE inhibitor, perindoprilat (hydrolyzed perindopril), perindopril and perindoprilat glucuronides, dehydrated perindopril and the diastereoisomers of dehydrated perindoprilat. In humans, hepatic esterase appears to be responsible for the hydrolysis of perindopril.

The active metabolite, perindoprilat, also exhibits multicompartment pharmacokinetics following the oral administration of Perindopril Erbumine. Formation of perindoprilat is gradual with peak plasma concentrations occurring between 3 and 7 hours. The subsequent decline in plasma concentration shows an apparent mean half-life of 3 to 10 hours for the majority of the elimination, with a prolonged terminal elimination half-life of 30 to 120 hours resulting from slow dissociation of perindoprilat from plasma/tissue ACE binding sites. During repeated oral once daily dosing with perindopril, perindoprilat accumulates about 1.5 to 2 fold and attains steady state plasma levels in 3 to 6 days. The clearance of perindoprilat and its metabolites is almost exclusively renal.

Elderly: Plasma concentrations of both perindopril and perindoprilat in elderly patients (greater than
70 years) are approximately twice those observed in younger patients, reflecting both increased conversion of perindopril to perindoprilat and decreased renal excretion of perindoprilat [see Dosage and Administration (2.1) and Use In Specific Populations (8.5)].

Heart Failure: Perindoprilat clearance is reduced in congestive heart failure patients, resulting in a 40% higher dose interval AUC.

Renal Impairment: With perindopril doses of 2 mg to 4 mg, perindoprilat AUC increases with decreasing renal function. At creatinine clearances of 30 to 80 mL/min, AUC is about double that at 100 mL/min. When creatinine clearance drops below 30 mL/min, AUC increases more markedly.

In a limited number of patients studied, perindopril clearance by dialysis ranged from about 40 to
80 mL/min. Perindoprilat clearance by dialysis ranged from about 40 to 90 mL/min [see Dosage and Administration (2.3)].

Hepatic Impairment: The bioavailability of perindoprilat is increased in patients with impaired hepatic function. Plasma concentrations of perindoprilat in patients with impaired liver function were about 50% higher than those observed in healthy subjects or hypertensive patients with normal liver function.

13 NONCLINICAL TOXICOLOGY

13.1 Carcinogenesis, Mutagenesis, Impairment of Fertility

Carcinogenicity: No evidence of carcinogenic effect was observed in studies in rats and mice when perindopril was administered at dosages up to 20 times (mg/kg) or 2 to 4 times (mg/m^2) the maximum proposed clinical doses (16 mg/day) for 104 weeks.

Mutagenesis: No genotoxic potential was detected for Perindopril Erbumine, perindoprilat and other metabolites in various in vitro and in vivo investigations, including the Ames test, the Saccharomyces cerevisiae D4 test, cultured human lymphocytes, TK ± mouse lymphoma assay, mouse and rat micronucleus tests and Chinese hamster bone marrow assay.

Impairment of Fertility: There was no meaningful effect on reproductive performance or fertility in the rat given up to 30 times (mg/kg) or 6 times (mg/m^2) the proposed maximum clinical dosage of Perindopril Erbumine during the period of spermatogenesis in males or oogenesis and gestation in females.

14 CLINICAL STUDIES

14.1 Hypertension

In placebo-controlled studies of perindopril monotherapy (2 mg to 16 mg once daily) in patients with a mean blood pressure of about 150/100 mm Hg, 2 mg had little effect, but doses of 4 mg to 16 mg lowered blood pressure. The 8 mg and 16 mg doses were indistinguishable, and both had a greater effect than the 4 mg dose. In these studies, doses of 8 mg and 16 mg per day gave supine, through blood pressure reductions of 9 to 15/5 to 6 mm Hg. When once daily and twice daily dosing were compared, the twice daily dosing regimen was generally slightly superior, but by not more than about 0.5 mm Hg to 1 mm Hg. After 2 mg to 16 mg doses of perindopril, the trough mean systolic and diastolic blood pressure effects were about 75 to 100% of peak effects.

Perindopril’s effects on blood pressure were similar when given alone or on a background of 25 mg hydrochlorothiazide In general, the effect of perindopril occurred promptly, with effects increasing slightly over several weeks.

Formal interaction studies of Perindopril Erbumine have not been carried out with antihypertensive agents other than thiazides. Limited experience in controlled and uncontrolled trials coadministering Perindopril Erbumine with a calcium channel blocker, a loop diuretic or triple therapy (beta-blocker, vasodilator and a diuretic), does not suggest any unexpected interactions. In general, ACE inhibitors have less than additive effects when given with beta-adrenergic blockers, presumably because both work in part through the renin-angiotensin system.

In uncontrolled studies in patients with insulin-dependent diabetes, perindopril did not appear to affect glycemic control. In long-term use, no effect on urinary protein excretion was seen in these patients.

The effectiveness of Perindopril Erbumine was not influenced by sex and it was less effective in black patients than in nonblack patients. In elderly patients (greater than or equal to 60 years), the mean blood pressure effect was somewhat smaller than in younger patients, although the difference was not significant.

14.2 Stable Coronary Artery Disease

The EURopean trial On reduction of cardiac events with Perindopril in stable coronary Artery disease (EUROPA) was a multicenter, randomized, double-blind and placebo-controlled study conducted in
12,218 patients who had evidence of stable coronary artery disease without clinical heart failure. Patients had evidence of coronary artery disease documented by previous myocardial infarction more than 3 months before screening, coronary revascularization more than 6 months before screening, angiographic evidence of stenosis (at least 70% narrowing of one or more major coronary arteries), or positive stress test in men with a history of chest pain. After a run-in period of 4 weeks during which all patients received perindopril 2 mg to 8 mg, the patients were randomly assigned to perindopril 8 mg once daily (n=6,110) or matching placebo (n=6,108). The mean follow-up was 4.2 years. The study examined the long-term effects of perindopril on time to first event of cardiovascular mortality, nonfatal myocardial infarction, or cardiac arrest in patients with stable coronary artery disease. The mean age of patients was 60 years; 85% were male, 92% were taking platelet inhibitors, 63% were taking β blockers, and 56% were taking lipid-lowering therapy. The EUROPA study showed that perindopril significantly reduced the relative risk for the primary endpoint events (Table 1). This beneficial effect is largely attributable to a reduction in the risk of nonfatal myocardial infarction. This beneficial effect of perindopril on the primary outcome was evident after about one year of treatment (Figure 1). The outcome was similar across all predefined subgroups by age, underlying disease or concomitant medication (Figure 2).

Table 1. Primary Endpoint and Relative Risk Reduction
 | Perindopril (N = 6,110) | Placebo (N = 6,108) | RRR (95% CI) | P
Combined Endpoint Cardiovascular mortality, nonfatal MI or cardiac arrest | 488 (8%) | 603 (9.9%) | 20% (9 to 29) | 0.0003
Component Endpoint Cardiovascular mortality | 215 (3.5%) | 249 (4.1%) | 14% (-3 to 28) | 0.107
Nonfatal MI | 295 (4.8%) | 378 (6.2%) | 22% (10 to 33) | 0.001
Cardiac arrest | 6 (0.1%) | 11 (0.2%) | 46% (-47 to 80) | 0.22

CI=confidence interval; RRR: relative risk reduction; MI: myocardial infarction

16 HOW SUPPLIED/STORAGE AND HANDLING

Tablets are oblong with a score on one side.

Tablets | Appearance | NDC (Bottles of 100)
4 mg | Pink, debossed “ACN 4” on unscored side | NDC 10135-0599-01
8 mg | Salmon-colored, debossed “ACN 8” on unscored side | NDC 10135-0600-01

Keep out of the reach of children.

Store at controlled room temperature 20° to 25°C (68° to 77°F) [see USP]. Protect from moisture.

17 PATIENT COUNSELING INFORMATION

Female patients of childbearing age should be told about the consequences of exposure to Perindopril Erbumine during pregnancy. Discuss treatment options with women planning to become pregnant. Patients should be asked to report pregnancies to their physicians as soon as possible.

Tell patients to report promptly any indication of infection (e.g., sore throat, fever) which could be a sign of neutropenia.

Manufactured by:
Patheon Pharmaceuticals, Inc.
Cincinnati, OH 45237 USA

Distributed by:
Marlex Pharmaceuticals, Inc.
New Castle, DE 19720

Rev. 05/15 LAN

PRINCIPAL DISPLAY PANEL

NDC 10135-0599-01
Perindopril
Erbumine Tablets
4 mg
Rx Only
100 TABLETS

PRINCIPAL DISPLAY PANEL

NDC 10135-0600-01
Perindopril
Erbumine Tablets
8 mg
Rx Only
100 TABLETS